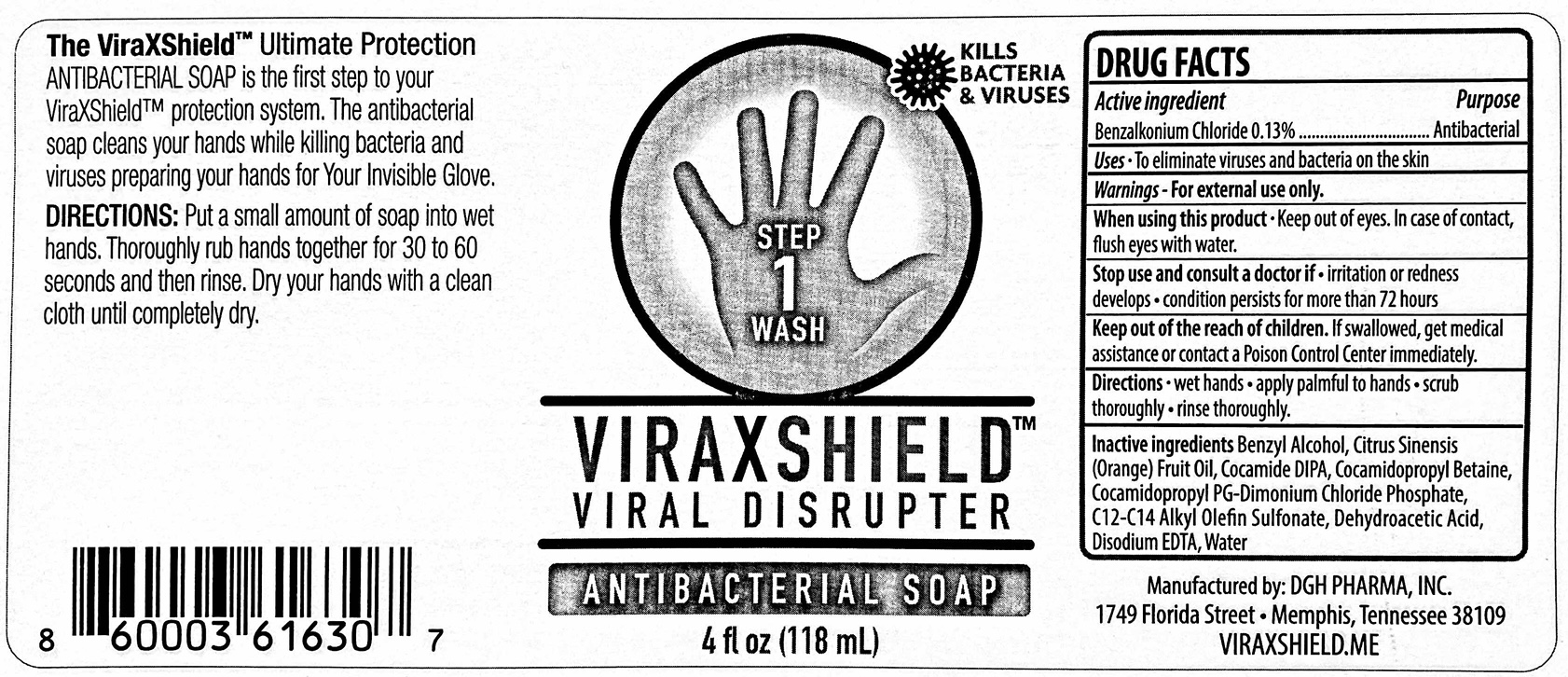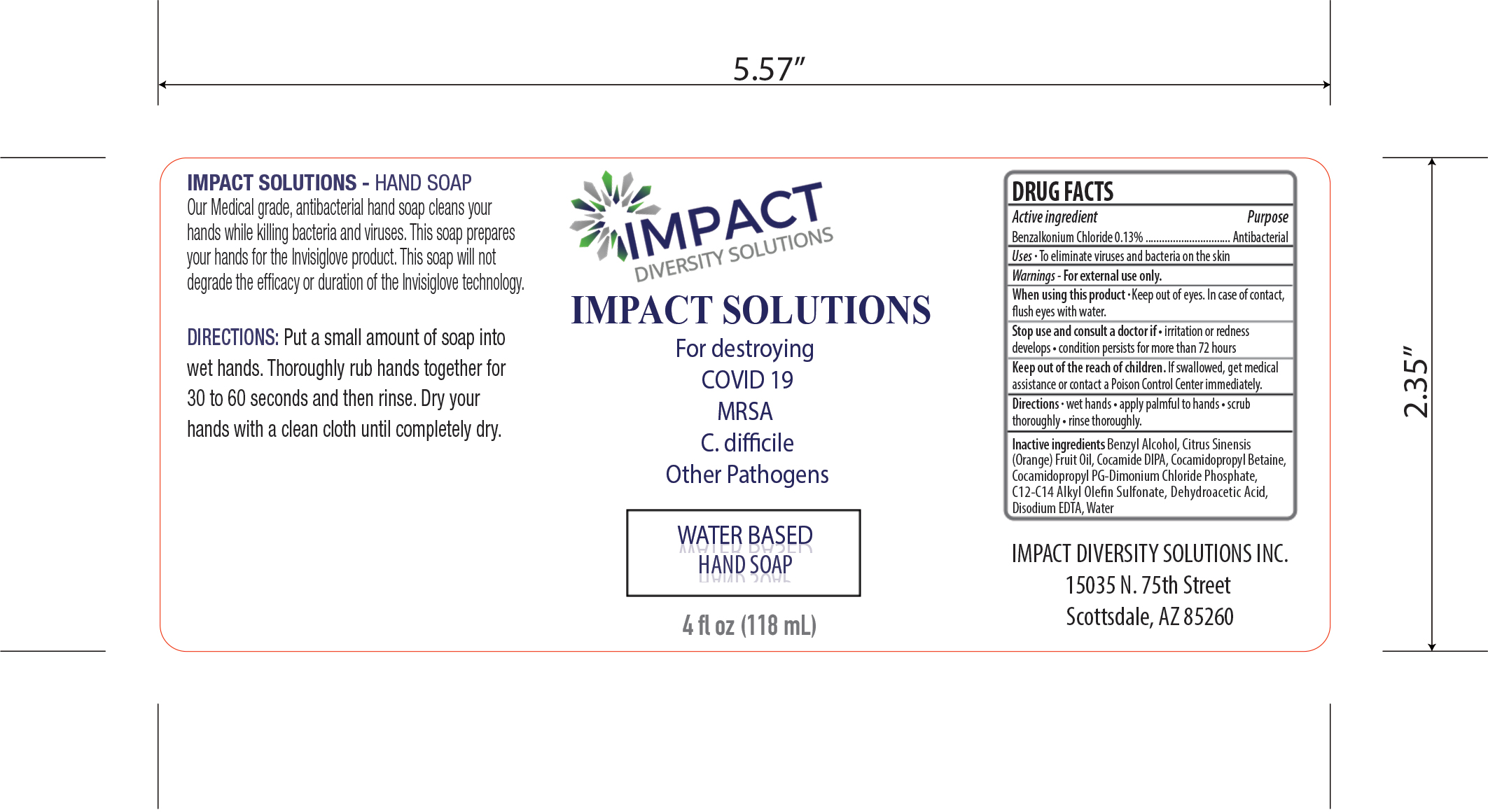 DRUG LABEL: Viraxshield
NDC: 77238-211 | Form: LIQUID
Manufacturer: DGH Pharma, Inc.
Category: otc | Type: HUMAN OTC DRUG LABEL
Date: 20201006

ACTIVE INGREDIENTS: BENZALKONIUM CHLORIDE 0.13 g/100 mL
INACTIVE INGREDIENTS: ANHYDROUS CITRIC ACID 0.25 g/100 mL; COCAMIDOPROPYL BETAINE 30 g/100 mL; WATER; COCO DIISOPROPANOLAMIDE 3.5 g/100 mL; SODIUM C12-14 OLEFIN SULFONATE 3.5 g/100 mL; EDETATE DISODIUM 0.05 g/100 mL; DEHYDROACETIC ACID 0.375 g/100 mL; BENZYL ALCOHOL 0.375 g/100 mL; ORANGE OIL 0.1 g/100 mL; COCAMIDOPROPYL PG-DIMONIUM CHLORIDE PHOSPHATE 0.75 g/100 mL

Antibacterial Hand Soap

Active Ingredient(s)

Benzalkonium Chloride 0.13% w/w. Purpose: Antibacterial

Purpose

Antibacterial hand soap

Use

To eliminate viruses and bacteria on the skin

Warnings

For external use only.

When using this product keep out of eyes. In case of contact, flush eyes with water.
Stop use and ask a doctor if irritation or redness develops - condition persists for more than 72 hours
Keep out of reach of children. If swallowed, get medical assistance or contact a Poison Control Center immediately.

Stop use and consult a doctor if irritation or redness develops - condition persists for more than 72 hours

Keep out of reach of children. If swallowed, get medical assistance or contact a Poison Control Center immediately.

Directions

- Wet hands
- apply palmful to hands
- scrub thoroughly
- rinse thoroughly

Inactive ingredients

Benzyl Alcohol, Citrus Sinensis (Orange) Fruit Oil, Coamide DIPA, Cocamidopropyl Betaine, Cocamidopropyl PG-Dimonium Chloride Phosphate, C12-C14 Alkyl Olefin Sulfonate, Dehydroacetic Acid, Disodium EDTA, Water